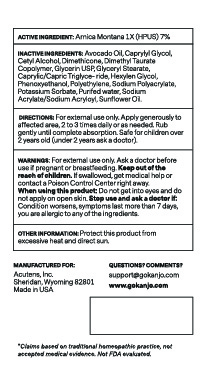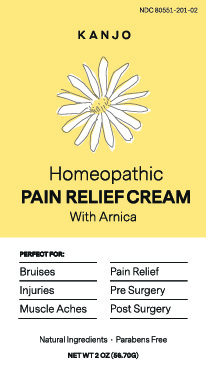 DRUG LABEL: Kanjo Homeopathic Pain Relief Cream
NDC: 80551-201 | Form: CREAM
Manufacturer: ACUTENS
Category: homeopathic | Type: HUMAN OTC DRUG LABEL
Date: 20201125

ACTIVE INGREDIENTS: ARNICA MONTANA 1 [hp_X]/1 g
INACTIVE INGREDIENTS: PHENOXYETHANOL; HIGH DENSITY POLYETHYLENE; AVOCADO OIL; TRICAPRIN; CAPRYLYL GLYCOL; CETYL ALCOHOL; POTASSIUM SORBATE; SODIUM ACRYLATE; SUNFLOWER OIL; GLYCERIN; SODIUM POLYACRYLATE (2500000 MW); WATER; HEXYLENE GLYCOL; GLYCERYL MONOSTEARATE; DIMETHICONE 100; SODIUM ACRYLATE/SODIUM ACRYLOYLDIMETHYLTAURATE COPOLYMER (4000000 MW)

Kanjo Homeopathic Pain Relief Cream

Kanjo Homeopathic Pain Relief Cream

Active Ingredient:

Arnica Montana 1X (HPUS) 7%

Purpose

Perfect for

Bruises

Injuries

Muscle Aches

Pain Relief

Pre Surgery

Post Surgery

Keep out of the reach of children. If swallowed, get medical help or contact a Poison Control Center right away.

Warnings:

For external use only. Ask a doctor before use if pregnant or breastfeeding.

When using this product

Do not get into eyes and do not apply to open skin.

Stop use and ask a doctor if:

Condition worsens, symptoms last more than 7 days, you are allergic to any of the ingredients

Other information:

Protect this product from excessive heat and direct sun.

Directions

For external use only. Apply generously to the affected area, 2 to 3 times daily or as needed. Rub gently until complete absorption.

Indications

Bruises, injuries, muscle aches, pain relief, pre-surgery, post-surgery

Inactive ingredients

Avocado Oil, Caprylyl Glycol, Cetyl Alcohol, Dimethicone, Dimethyl Taurate Copolymer, Glycerin
USP, Glyceryl Stearate, Caprylic/Capric Triglyceride, Hexylen Glycol, Phenoxyethanol, Polyethylene,
Sodium Polyacrylate, Potassium Sorbate, Purified Water, Sodium Acrylate/Sodium Acryloyl, Sunflower oil.

Warnings

For external use only. Ask a doctor before use if pregnant or breastfeeding. Keep out of the reach of
children. If swallowed, get medical help or contact a Poison Control Center right away.

Kanjo Homeopathic Pain Relief Cream

pain-relief-cream-front.jpg

Kanjo Homeopathic Pain Relief Cream

pain-relief-cream-back.jpg